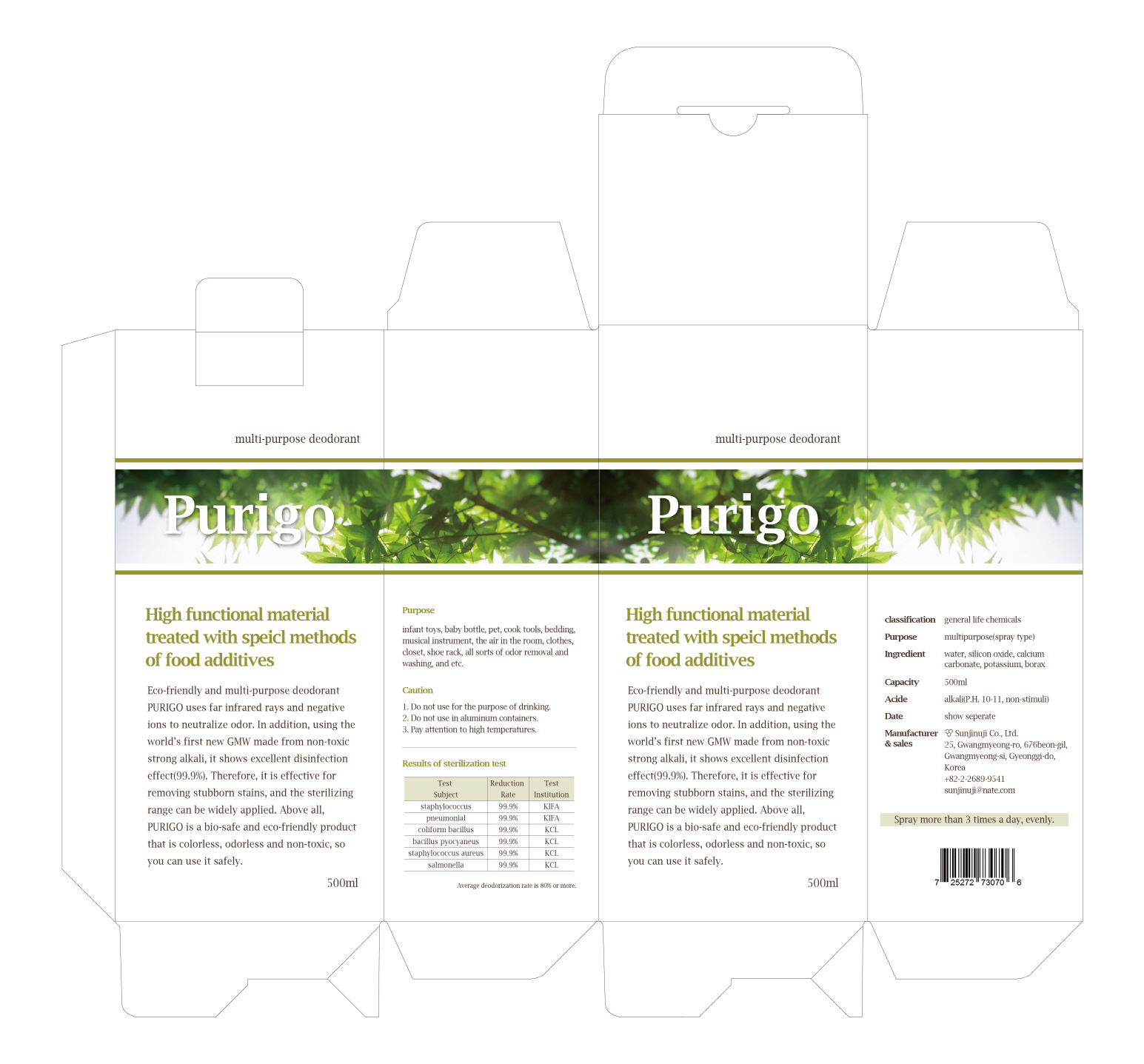 DRUG LABEL: Purigo
NDC: 71710-0001 | Form: LIQUID
Manufacturer: Sun Jin Yu Ji Co
Category: otc | Type: HUMAN OTC DRUG LABEL
Date: 20170906

ACTIVE INGREDIENTS: POTASSIUM 9.3 g/100 mL; SILICON DIOXIDE 31 g/100 mL; CALCIUM CARBONATE 18 g/100 mL
INACTIVE INGREDIENTS: WATER

Active ingredient

Silicon oxide, Potassium, Borax, Calcium carbonate

Purpose

Disinfectant Deodorant

Use

Deodrant of multi-purpose (infant toys, baby bottle, pet, cook tools, bedding, musical instrument, the air in the room, clothes, closet, shoe rack, all sorts of odor removal and washing, and etc.)

WARNINGS

1. Do not use for the purpose of drinking.
2. Do not use in aluminum containers.
3. Pay attention to high temperatures.
4. Carefully release the lid before opening.
5. Put in the shade.

Keep out of reach of children

Directions

Spray more than 3 times a day, evenly.

INACTIVE INGREDIENT

barley stone, zeolite, germanium, ferric chloride, sugar, additive, distilled water